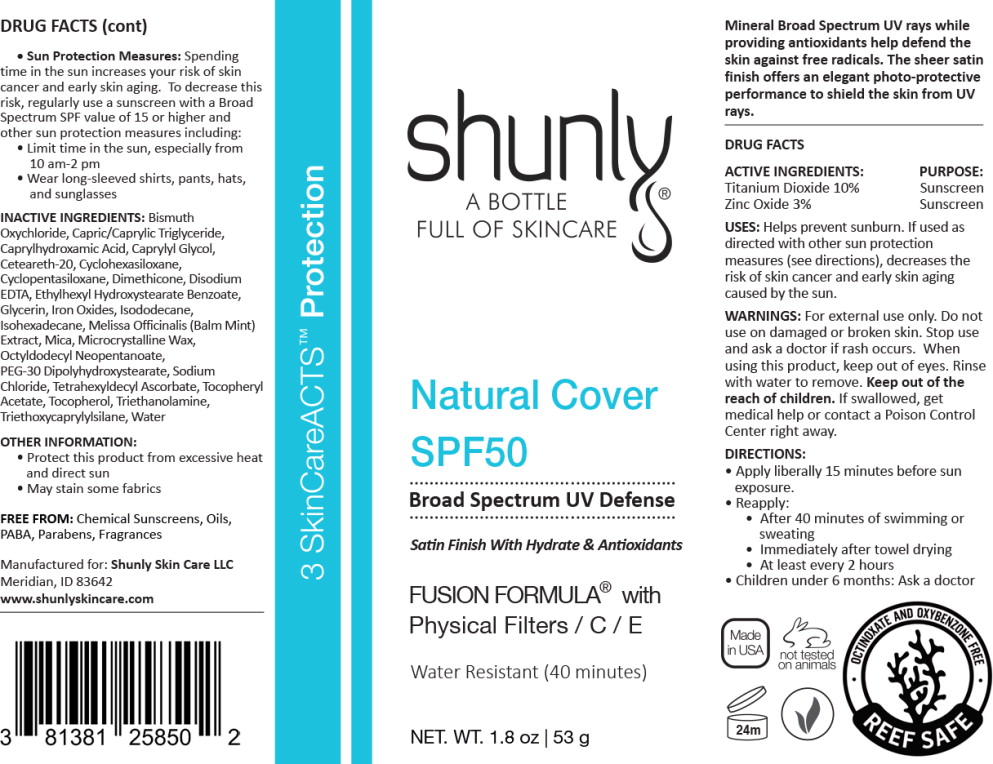 DRUG LABEL: Shunly Natural Cover SPF50
NDC: 81381-258 | Form: CREAM
Manufacturer: Shunly Skin Care
Category: otc | Type: HUMAN OTC DRUG LABEL
Date: 20251208

ACTIVE INGREDIENTS: TITANIUM DIOXIDE 100 mg/1 g; ZINC OXIDE 30 mg/1 g
INACTIVE INGREDIENTS: BISMUTH OXYCHLORIDE; MEDIUM-CHAIN TRIGLYCERIDES; CAPRYLHYDROXAMIC ACID; CAPRYLYL GLYCOL; POLYOXYL 20 CETOSTEARYL ETHER; CYCLOMETHICONE 6; CYCLOMETHICONE 5; DIMETHICONE; EDETATE DISODIUM ANHYDROUS; ETHYLHEXYL HYDROXYSTEARATE BENZOATE; GLYCERIN; FERRIC OXIDE RED; FERRIC OXIDE YELLOW; FERROSOFERRIC OXIDE; ISODODECANE; ISOHEXADECANE; MELISSA OFFICINALIS WHOLE; MICA; MICROCRYSTALLINE WAX; OCTYLDODECYL NEOPENTANOATE; PEG-30 DIPOLYHYDROXYSTEARATE (4000 MW); SODIUM CHLORIDE; TETRAHEXYLDECYL ASCORBATE; .ALPHA.-TOCOPHEROL ACETATE; TOCOPHEROL; TROLAMINE; TRIETHOXYCAPRYLYLSILANE; WATER

ACTIVE INGREDIENTS:

Titanium Dioxide 10%

Zinc Oxide 3%

PURPOSE:

Sunscreen

Sunscreen

USES:

Helps prevent sunburn. If used as directed with other sun protection measures (see directions), decreases the risk of skin cancer and early skin aging caused by the sun.

WARNINGS:

For external use only.

Do not use on damaged or broken skin.

Stop use and ask a doctor if rash occurs.

When using this product, keep out of eyes. Rinse with water to remove.

KEEP OUT OF REACH OF CHILDREN

Keep out of the reach of children.If swallowed, get medical help or contact a Poison Control Center right away.

DIRECTIONS:

- Apply liberally 15 minutes before sun exposure.
- Reapply:
  - After 40 minutes of swimming or sweating
  - Immediately after towel drying
  - At least every 2 hours
- Children under 6 months: Ask a doctor
- Sun Protection Measures:Spending time in the sun increases your risk of skin cancer and early skin aging. To decrease this risk, regularly use a sunscreen with a Broad Spectrum SPF value of 15 or higher and other sun protection measures including:
  - Limit time in the sun, especially from 10 am-2 pm
  - Wear long-sleeved shirts, pants, hats, and sunglasses

INACTIVE INGREDIENTS:

Bismuth Oxychloride, Capric/Caprylic Triglyceride, Caprylhydroxamic Acid, Caprylyl Glycol, Ceteareth-20, Cyclohexasiloxane, Cyclopentasiloxane, Dimethicone, Disodium EDTA, Ethylhexyl Hydroxystearate Benzoate, Glycerin, Iron Oxides, Isododecane, Isohexadecane, Melissa Officinalis (Balm Mint) Extract, Mica, Microcrystalline Wax, Octyldodecyl Neopentanoate, PEG-30 Dipolyhydroxystearate, Sodium Chloride, Tetrahexyldecyl Ascorbate, Tocopheryl Acetate, Tocopherol, Triethanolamine, Triethoxycaprylylsilane, Water

OTHER INFORMATION:

- Protect this product from excessive heat and direct sun
- May stain some fabrics

FREE FROM:Chemical Sunscreens, Oils, PABA, Parabens, Fragrances

Manufactured for: Shunly Skin Care LLC

Meridian, ID 83642

www.shunlyskincare.com

Keep out of the reach of children.

Principal Display Panel – 53 g Bottle Label

shunly®

A BOTTLE
FULL OF SKINCARE

Natural Cover

SPF50

Broad Spectrum UV Defense

Satin Finish With Hydrate & Antioxidants

FUSION FORMULA® with
Physical Filters / C / E

Water Resistant (40 minutes)

NET. WT. 1.8 oz | 53 g